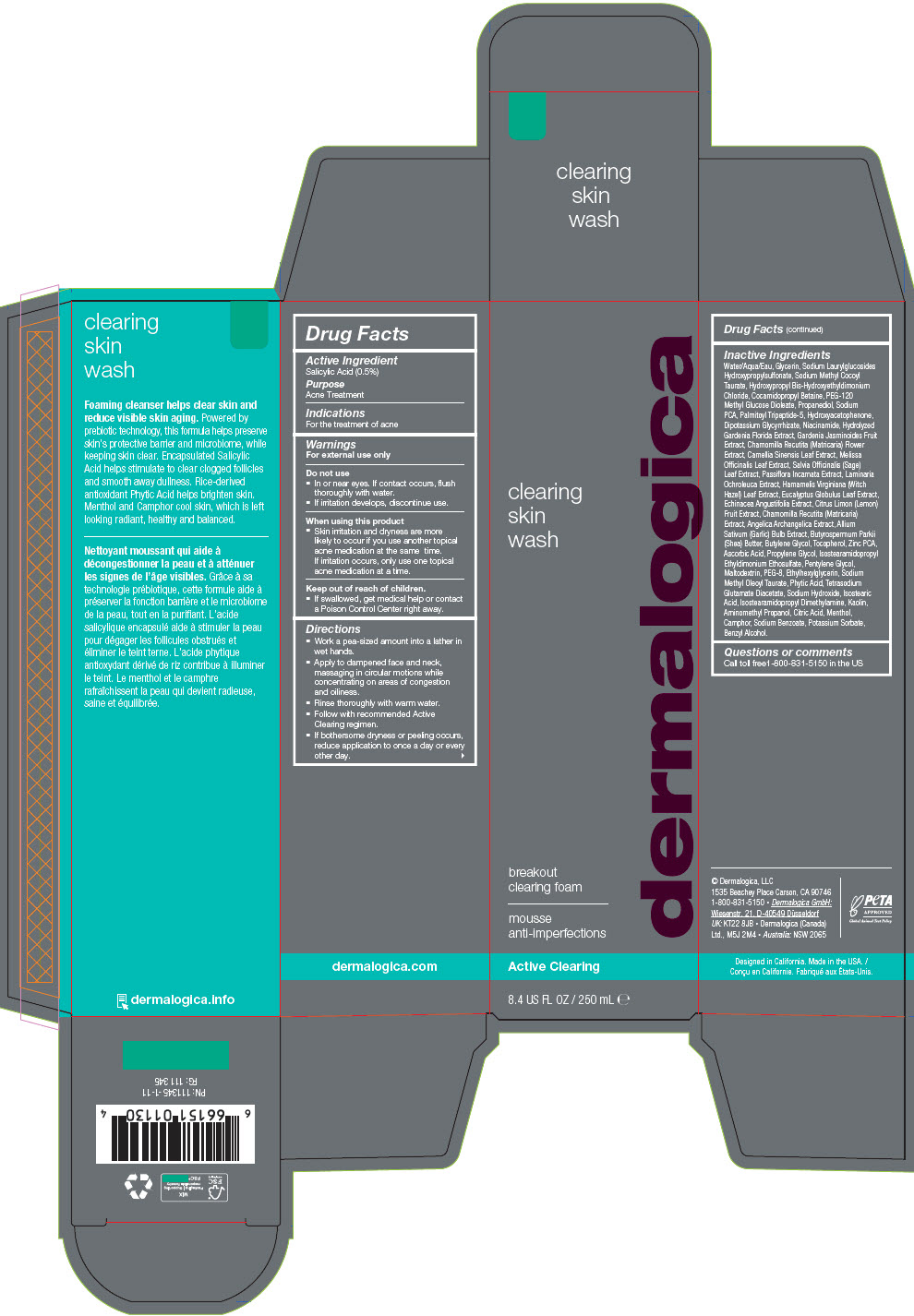 DRUG LABEL: Clearing Skin Wash
NDC: 68479-942 | Form: LIQUID
Manufacturer: Dermalogica, LLC.
Category: otc | Type: HUMAN OTC DRUG LABEL
Date: 20241030

ACTIVE INGREDIENTS: Salicylic Acid 0.501 mg/100 mL
INACTIVE INGREDIENTS: WATER; Glycerin; Sodium Laurylglucosides Hydroxypropylsulfonate; Sodium Methyl Cocoyl Taurate; Hydroxypropyl Bis-Hydroxyethyldimonium Chloride; Cocamidopropyl Betaine; PEG-120 Methyl Glucose Dioleate; Propanediol; SODIUM PIDOLATE; Sodium Methyl Oleoyl Taurate; Propylene Glycol; Butylene Glycol; Hydroxyacetophenone; FYTIC ACID; Isostearamidopropyl Ethyldimonium Ethosulfate; POLYETHYLENE GLYCOL 400; GLYCYRRHIZINATE DIPOTASSIUM; Tetrasodium Glutamate Diacetate; AMINOMETHYLPROPANOL; CAMPHOR (NATURAL); LEVOMENTHOL; Niacinamide; Sodium Hydroxide; Pentylene Glycol; MELISSA OFFICINALIS LEAF; GARLIC; CHAMOMILE; LEMON; ECHINACEA ANGUSTIFOLIA WHOLE; EUCALYPTUS GLOBULUS LEAF; HAMAMELIS VIRGINIANA LEAF; LAMINARIA OCHROLEUCA; PASSIFLORA INCARNATA WHOLE; SAGE OIL; Maltodextrin; Ethylhexylglycerin; Potassium Sorbate; Sodium Benzoate; Isostearamidopropyl Dimethylamine; Isostearic Acid; GARDENIA JASMINOIDES WHOLE; Tocopherol; GARDENIA JASMINOIDES FRUIT; Ascorbic Acid; SHEA BUTTER; Kaolin; ZINC PIDOLATE; Palmitoyl Tripeptide-5; GREEN TEA LEAF; CITRIC ACID MONOHYDRATE; ANGELICA ARCHANGELICA WHOLE

Clearing Skin Wash

Drug Facts

Active Ingredient

Salicylic Acid (0.5%)

Purpose

Acne Treatment

Indications

For the treatment of acne

Warnings

For external use only

Do not use

- In or near eyes. If contact occurs, flush thoroughly with water.
- If irritation develops, discontinue use.

When using this product

- Skin irritation and dryness are more likely to occur if you use another topical acne medication at the same time. If irritation occurs, only use one topical acne medication at a time.

Keep out of reach of children.

- If swallowed, get medical help or contact a Poison Control Center right away.

Directions

- Work a pea-sized amount into a lather in wet hands.
- Apply to dampened face and neck, massaging in circular motions while concentrating on areas of congestion and oiliness.
- Rinse thoroughly with warm water.
- Follow with recommended Active Clearing regimen.
- If bothersome dryness or peeling occurs, reduce application to once a day or every other day.

Inactive Ingredients

Water/Aqua/Eau, Glycerin, Sodium Laurylglucosides Hydroxypropylsulfonate, Sodium Methyl Cocoyl Taurate, Hydroxypropyl Bis-Hydroxyethyldimonium Chloride, Cocamidopropyl Betaine, PEG-120 Methyl Glucose Dioleate, Propanediol, Sodium PCA, Palmitoyl Tripeptide-5, Hydroxyacetophenone, Dipotassium Glycyrrhizate, Niacinamide, Hydrolyzed Gardenia Florida Extract, Gardenia Jasminoides Fruit Extract, Chamomilla Recutita (Matricaria) Flower Extract, Camellia Sinensis Leaf Extract, Melissa Officinalis Leaf Extract, Salvia Officinalis (Sage) Leaf Extract, Passiflora Incarnata Extract, Laminaria Ochroleuca Extract, Hamamelis Virginiana (Witch Hazel) Leaf Extract, Eucalyptus Globulus Leaf Extract, Echinacea Angustifolia Extract, Citrus Limon (Lemon) Fruit Extract, Chamomilla Recutita (Matricaria) Extract, Angelica Archangelica Extract, Allium Sativum (Garlic) Bulb Extract, Butyrospermum Parkii (Shea) Butter, Butylene Glycol, Tocopherol, Zinc PCA, Ascorbic Acid, Propylene Glycol, Isostearamidopropyl Ethyldimonium Ethosulfate, Pentylene Glycol, Maltodextrin, PEG-8, Ethylhexylglycerin, Sodium Methyl Oleoyl Taurate, Phytic Acid, Tetrasodium Glutamate Diacetate, Sodium Hydroxide, Isostearic Acid, Isostearamidopropyl Dimethylamine, Kaolin, Aminomethyl Propanol, Citric Acid, Menthol, Camphor, Sodium Benzoate, Potassium Sorbate, Benzyl Alcohol.

Questions or comments

Call toll free1-800-831-5150 in the US

PRINCIPAL DISPLAY PANEL - 250 mL Bottle Carton

clearing
skin
wash

dermalogica

breakout
clearing foam

Active Clearing

8.4 US FL OZ / 250 mL ℮